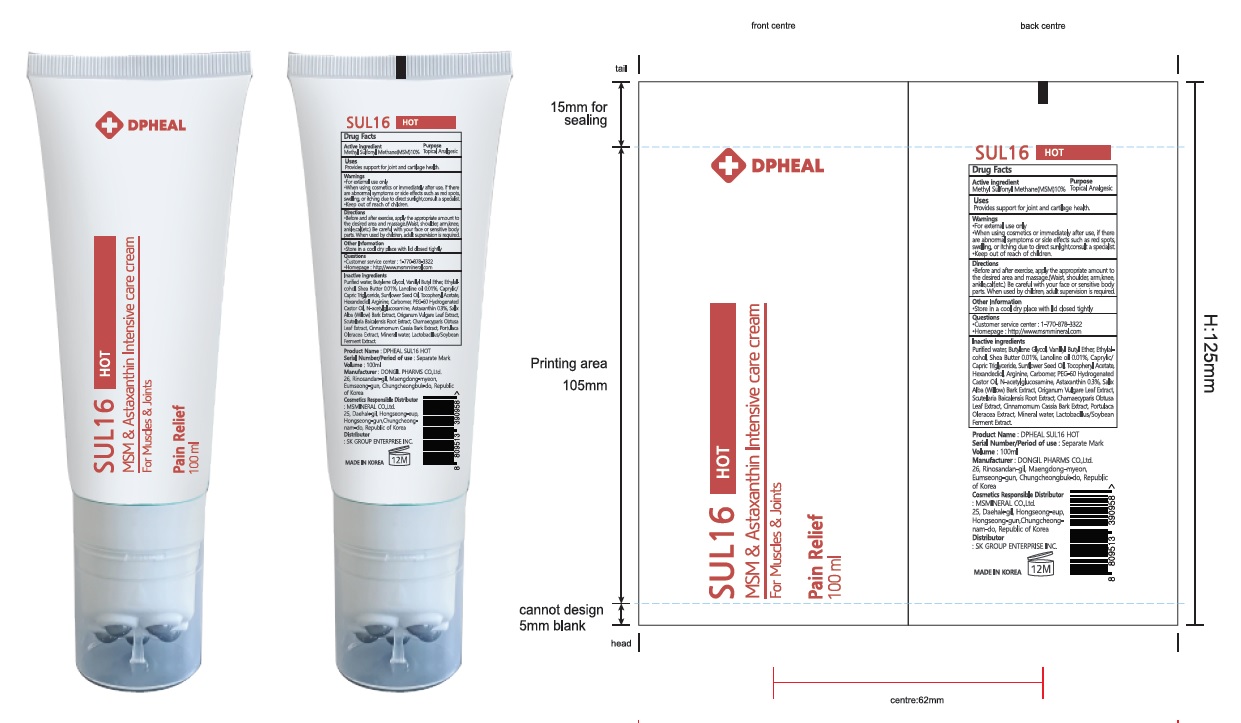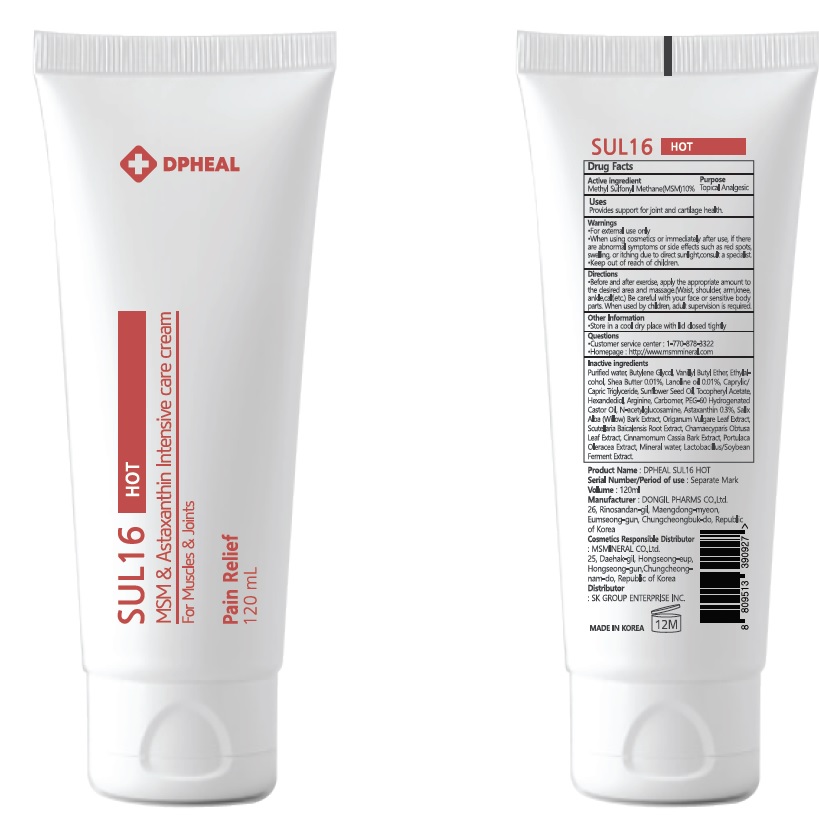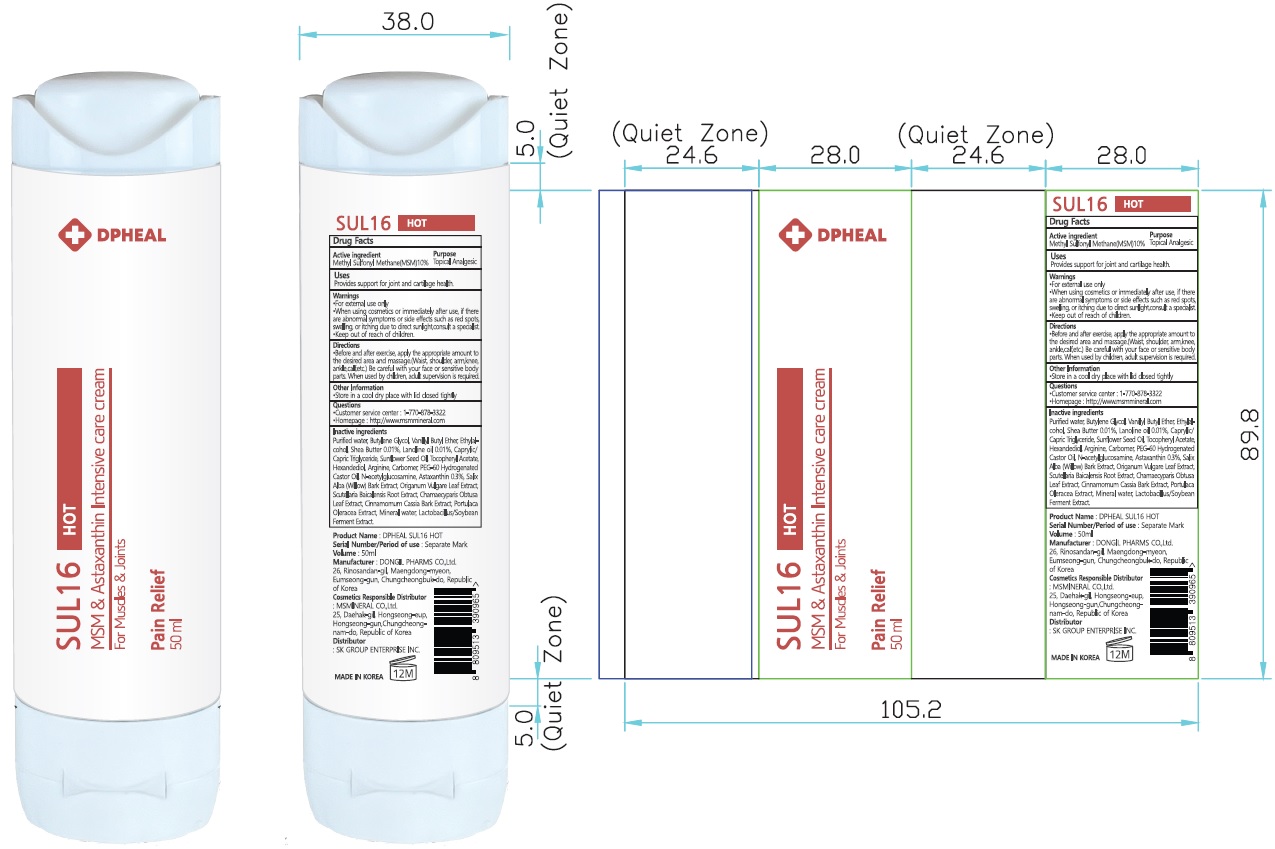 DRUG LABEL: DPHEAL SUL 16 HOT
NDC: 82409-020 | Form: GEL
Manufacturer: MSMINERAL CO.,Ltd.
Category: otc | Type: HUMAN OTC DRUG LABEL
Date: 20211126

ACTIVE INGREDIENTS: DIMETHYL SULFONE 10.0 g/100 mL
INACTIVE INGREDIENTS: Water; Butylene Glycol; ALCOHOL

ACTIVE INGREDIENT

Methyl Sulfonyl Methane(MSM) 10%

INACTIVE INGREDIENTS

Purified water, Butylene Glycol, Vanillyl Butyl Ether, Ethylalcohol, Shea Butter 0.01%, Lanoline oil 0.01%, Caprylic/Capric Triglyceride, Sunflower Seed Oil, Tocopheryl Acetate, Hexandediol, Arginine, Carbomer, PEG-60 Hydrogenated Castor Oil, N-acetylglucosamine, Astaxanthin 0.3%, Salix Alba (Willow) Bark Extract, Origanum Vulgare Leaf Extract, Scutellaria Baicalensis Root Extract, Chamaecyparis Obtusa Leaf Extract, Cinnamomum Cassia Bark Extract, Portulaca Oleracea Extract, Mineral water, Lactobacillus/Soybean Ferment Extract

PURPOSE

Topical Analgesic

Uses

■ Provides support for joint and cartilage health.

WARNINGS

■ For external use only
■ When using cosmetics or immediately after use, if there are abnormal symptoms or side effects such as red spots, swelling, or itching due to direct sunlight, consult a specialist.
■ Keep out of reach of children

KEEP OUT OF REACH OF CHILDREN

Directions

■ Before and after exercise, apply the appropriate amount to the desired area and massage.
(Waist, shoulder, arm, knee, ankle, calf, etc.) Be careful with your face or sensitive body parts.When used by children, adult supervision is required.

Other Information

■ Store in a cool dry place with lid closed tightly

Questions

■ Customer service center : 1-770-878-3322
■ Homepage : http://www.msmmineral.com